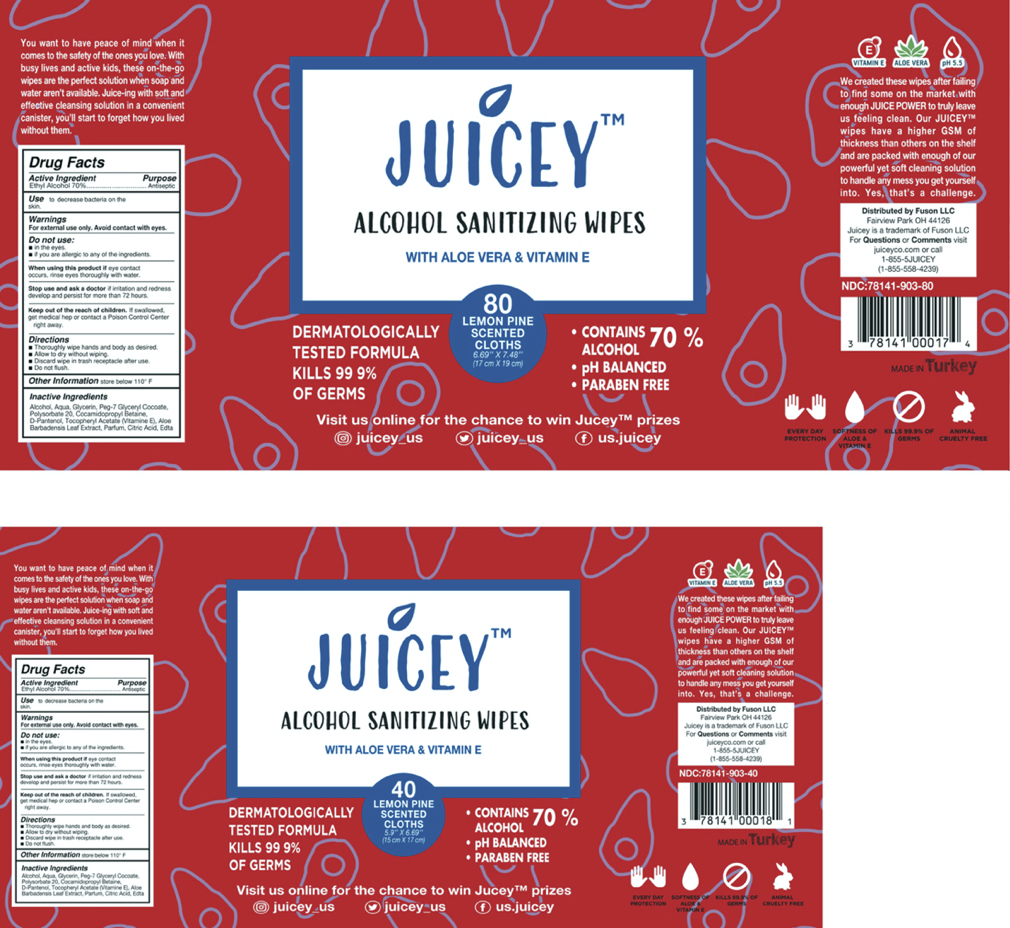 DRUG LABEL: Juicey Alcohol Wipes
NDC: 80783-903 | Form: CLOTH
Manufacturer: MEHMET YILDIZ YILDIZ KOZMETIK
Category: otc | Type: HUMAN OTC DRUG LABEL
Date: 20201005

ACTIVE INGREDIENTS: ALCOHOL 3.059 mL/4.37 mL
INACTIVE INGREDIENTS: WATER; EDETIC ACID; LEMON OIL, DISTILLED; PEG-7 GLYCERYL COCOATE; .ALPHA.-TOCOPHEROL ACETATE; DEXPANTHENOL; ANHYDROUS CITRIC ACID; COCAMIDOPROPYL BETAINE; GLYCERIN; POLYSORBATE 20; ALOE VERA LEAF

Active Ingredient

Ethyl Alcohol (Ethanol) 70% v/v - antispectic

Inactive Ingredients

peg-7 glyceryl cocoate, edetic acid, anhydrous citric acid, polysorbate 20, cocamidopropyl betaine, distilled lemon oil, glycerin, dexpanthenol, water, aloe barbadensis leaf extract, tocopheryl acetate (vitamin E)

Purpose

Antiseptic- antibacterial hand towelettes

Use

Wipes used on hands to reduce bacteria on the skin

Warnings

Highly flamable liquid. For external use only; do not ingest. Do not use near eyes. Keep away from flame and direct sunlight. Do not eat, drink, or smoke during use. If redness or irritation occurs and persists for longer than 48 hours, seek medical attention.

Do not use if allgeric to any of its ingredients. Do not use on children under 2 months of age. Do not use while eating, drinking, or smoking. Do not use near eyes or open wounds.

When Using

If ingested, contact a poison control center immediately. If eye contact occurs, remove any contact lenses and flush eyes with water repeatedly

Stop Use

Stop use if redness or irritation occurs.

KEEP OUT OF REACH OF CHILDREN

Store in places out of reach to children. Supervise use by children under the age of 6. If swallowed, contact a poison control center or seek medial attention immediately.

Directions

Open top hard plastic flip cover and remove one towelette at a time and then securely close the packaging. Wipe towlettes on the desired area of the body and allow to dry. Do not flush towelettes.

Storage

Keep away from flame and direct sunlight. Store in a cool, dry place out of reach of children. Do not store near food, drinks, or animal feed. Store tightly in its original packaging.

Package Label

40 Count Canister NDC: 80783-903-40

80 Count Canister NDC: 80783-903-80